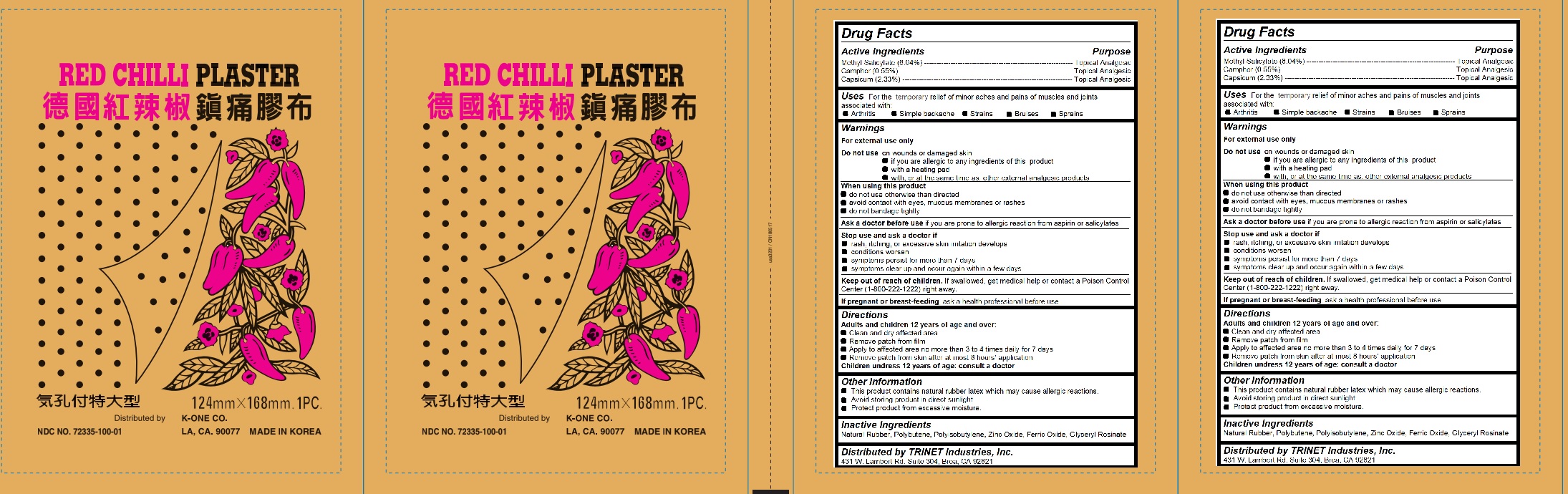 DRUG LABEL: Red Chilli Plaster
NDC: 72335-100 | Form: PATCH
Manufacturer: Trinet Industries Inc
Category: otc | Type: HUMAN OTC DRUG LABEL
Date: 20191220

ACTIVE INGREDIENTS: METHYL SALICYLATE 273 mg/4516 mg; CAMPHOR (NATURAL) 25 mg/4516 mg; CAPSICUM 105 mg/4516 mg
INACTIVE INGREDIENTS: NATURAL LATEX RUBBER; POLYBUTENE (1400 MW)

Red Chilli Plaster

Active ingredients

Methyl Salicylate (6.04%) -------------------------------------------------------------- Topical Analgesic

Camphor (0.55%) ------------------------------------------------------------------------ Topical Analgesic

Capsicum (2.33%) -----------------------------------------------------------------------

Uses

For the temporarily relief of minor aches and pains of muscles and joints associated with:

Arthritis Simple backache Strains Bruises Sprains

Purpose

Topical Analgesic

Uses

For the temporary relief of minor aches and pains of muscles and joints associated with:

Arthritis Simple backache Strains Bruises Sprains

Keep out of reach of children.

If swallowed, get medical help or contact a Poison Control Center (1-800-222-1222) right away.

Inactive Ingredients

Natural Rubber, Polybutene, Polyisobutylene, Zinc Oxide, Ferric Oxide, Glyceryl Rosinate

Warnings

For external use only